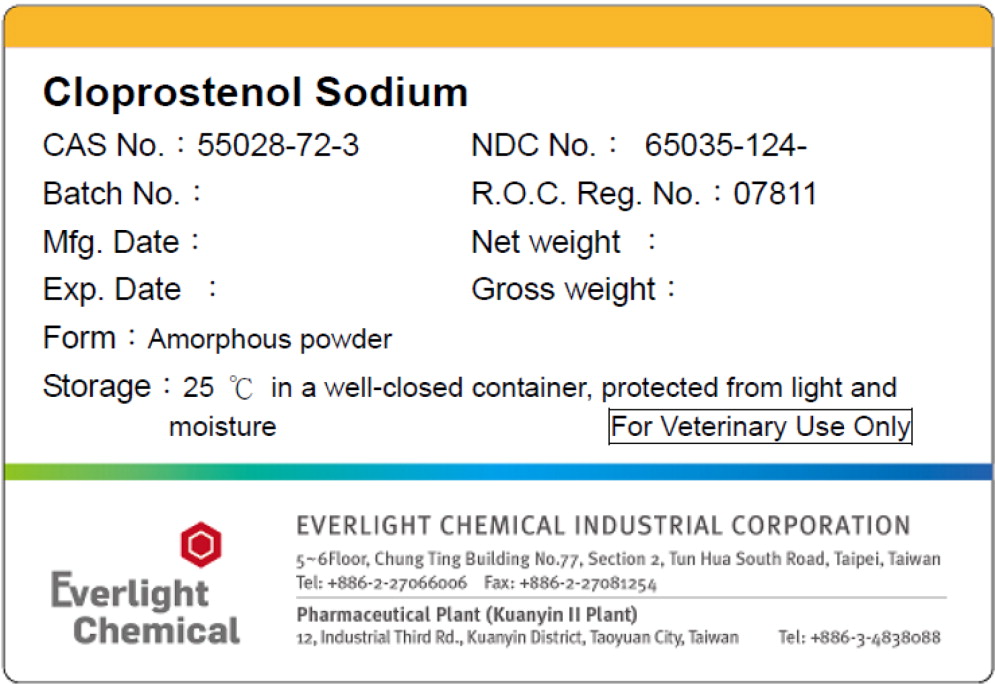 DRUG LABEL: Cloprostenol Sodium
NDC: 65035-124 | Form: POWDER
Manufacturer: Everlight Chemical Industrial Corporation Kuanyin II Plant
Category: other | Type: BULK INGREDIENT - ANIMAL DRUG
Date: 20200211

ACTIVE INGREDIENTS: Cloprostenol Sodium 1 g/1 g

Principal Display Panel - Bottle Label

Cloprostenol Sodium

CAS No.: 55028-72-3 NDC No.: 65035-124-

Batch No.: R.O.C. Reg No.: 07811

Mfg. Date: Net Weight:

Exp. Date: Gross Weight:

Form: Amorphous powder

Storage: 25 °C in a well-closed container,
protected from light and moisture

For Veterinary Use Only

EVERLIGHT CHEMICAL INDUSTRIAL CORPORATION

5~6 Floor, Chung Ting Building No. 77, Section 2, Tun Hua South Road, Taipei, Taiwan
Tel: +886-2-27066006 Fax +886-2-27081254

Pharmaceutical Plant Tel: +886-3-4838088
12, Industrial Third Rd., Kuanyin District, Taoyuan City, Taiwan